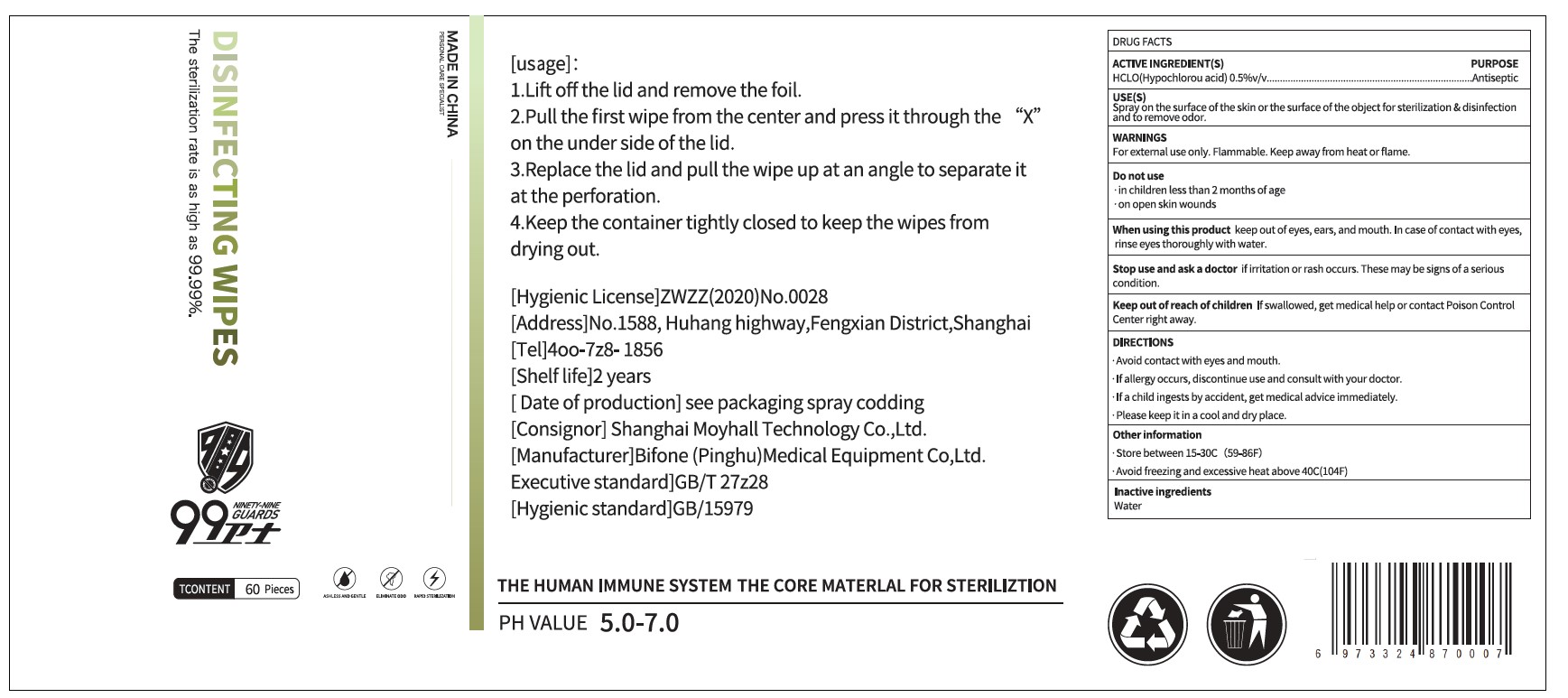 DRUG LABEL: DISINFECTING WIPES
NDC: 94973-002 | Form: PATCH
Manufacturer: Bifone (Pinghu) Medical Equipment Co., Ltd
Category: otc | Type: HUMAN OTC DRUG LABEL
Date: 20201119

ACTIVE INGREDIENTS: HYPOCHLOROUS ACID 0.5 g/100 g
INACTIVE INGREDIENTS: WATER

DISINFENTING WIPES

Active Ingredient(s)

HCLO (Hypochlorou) 0.5% v/v. Purpose: Antiseptic

Purpose

Antiseptic, Hand Sanitizer

Use

scrub the surface of the skin or the surface of the object for sterilization & disinfention and to remove odor.

Warnings

For external use only. Flammable. Keep away from heat or flame

Do not use

- in children less than 2 months of age
- on open skin wounds

When using this product keep out of eyes, ears, and mouth. In case of contact with eyes, rinse eyes thoroughly with water.
Stop use and ask a doctor if irritation or rash occurs. These may be signs of a serious condition.
Keep out of reach of children. If swallowed, get medical help or contact a Poison Control Center right away.

Stop use and ask a doctor if irritation or rash occurs. These may be signs of a serious condition.

Keep out of reach of children. If swallowed, get medical help or contact a Poison Control Center right away.

Directions

Avoid contact with eyes and mouth.

If allergy occurs,discontinue use and consult with your doctor.

If a child ingests by accident, get medical advice immediately.

Please keep it in a cool and dry place

Other information

- Store between 15-30C (59-86F)
- Avoid freezing and excessive heat above 40C (104F)

Inactive ingredients

water